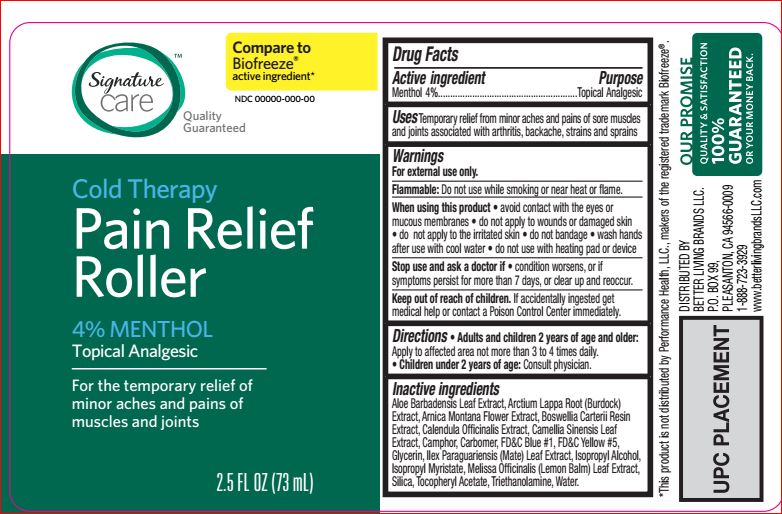 DRUG LABEL: Pain Relief Roller
NDC: 21130-764 | Form: GEL
Manufacturer: Better Living
Category: otc | Type: HUMAN OTC DRUG LABEL
Date: 20180118

ACTIVE INGREDIENTS: Menthol 4 g/100 mL
INACTIVE INGREDIENTS: ALOE VERA LEAF; ARCTIUM LAPPA ROOT; ARNICA MONTANA FLOWER; FRANKINCENSE; CALENDULA OFFICINALIS FLOWER; GREEN TEA LEAF; CAMPHOR (SYNTHETIC); Glycerin; ILEX PARAGUARIENSIS LEAF; Isopropyl Alcohol; Isopropyl Myristate; MELISSA OFFICINALIS LEAF; SILICON DIOXIDE; .ALPHA.-TOCOPHEROL ACETATE; TROLAMINE; WATER

Drug Facts

Active ingredient Purpose
Menthol 4%...............................................................Topical anesthetic

Uses

For the temporary relief from minor aches and pains of soar muscles and joints associated with arthritis, backache, strains and sprains

Warnings
For external use only.

Flammable: Do not use while smoking or near heat or flame
When using this product • avoid contact with eyes or mucouse membranes•do not apply to wounds or damaged skin • do not apply to the irritated skin • do not bandage • wash hands after use with cool water • do not use with heating pad or device.

Stop use and ask a doctor if • condition worsens • symptoms persist for more than 7 days or clear up and occur again within
a few days.

Keep out of reach of children. If swallowed, get medical help or contact a Poison Control Center immediately

Directions
Shake well. Adults and children 2 years of age and older: Apply to affected area not more than 3 to 4 times daily. Children under 2 years of
age: consult a doctor.

Inactive ingredients

Aloe Barbadensis Leaf Extract
Arctium Lappa Root (Burdock) Extract
Arnica Montana Flower Extract
Boswellia Carterii Resin Extract
Calendula Officinalis Extract
Camellia Sinensis Leaf Extract
Camphor
Carbomer
FD&C Blue #1
FD&C Yellow #5
Glycerin
Ilex Paraguariensis (Mate) Leaf Extract
Isopropyl Alcohol
Isopropyl Myristate
Melissa Officinalis (Lemon Balm) Leaf Extract
Silica
Tocopheryl Acetate
Triethanolamine
Water